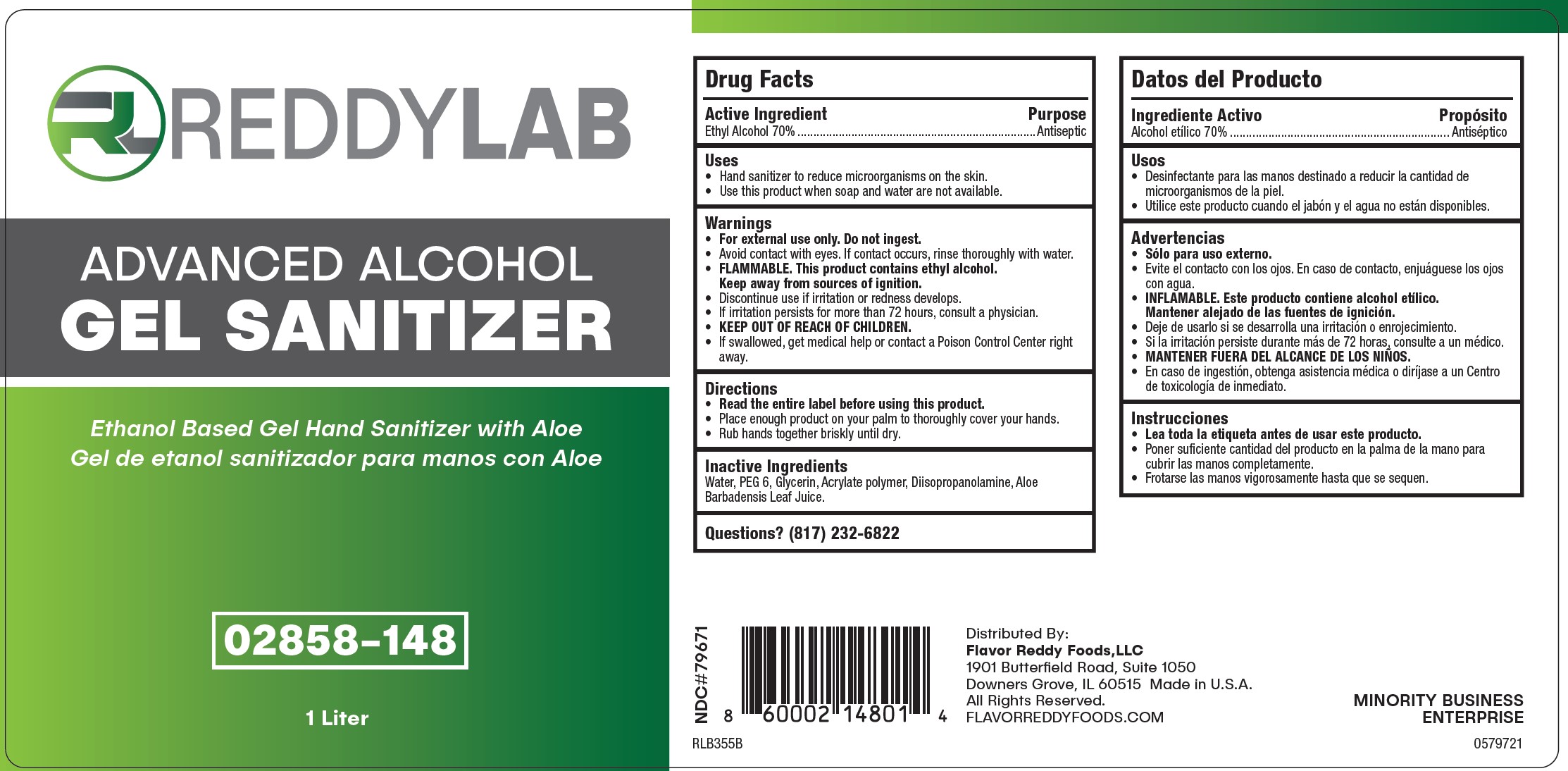 DRUG LABEL: Reddy Lab Advanced Alcohol Gel Sanitizer
NDC: 79671-797 | Form: GEL
Manufacturer: Flavor Reddy Foods, LLC
Category: otc | Type: HUMAN OTC DRUG LABEL
Date: 20251008

ACTIVE INGREDIENTS: ALCOHOL 0.7 mL/1 mL
INACTIVE INGREDIENTS: WATER; DIISOPROPANOLAMINE; ALOE VERA LEAF; POLYETHYLENE GLYCOL, UNSPECIFIED; ACRYLATES/VINYL ISODECANOATE CROSSPOLYMER (10000 MPA.S NEUTRALIZED AT 0.5%); GLYCERIN

Reddy Lab Advanced Alcohol Gel Sanitizer

Active Ingredient

Ethyl Alcohol 70%

WARNINGS

Wanings

- For external use only. Do not ingest
- Avoid contact with eyes. If contact occurs, rinse thoroughly with water.
- FLAMMABLE. This product contains ethyl alcohol.
- Keep away from sources of ignition.
- Discontinue use if irritation or redness develops.
- If irritation persists for more than 72 hours, contact a physician.
- KEEP OUT OF THE REACH OF CHILDREN
- IF swallowed, get medical help or contact a Poison Control Center right away.

INACTIVE INGREDIENT

Water, Glycerin, PEG-6 (and) AMP - Acrylates/Vinyl Isodecanoate Crosspolymer, Diisopropanolamine, Aloe Barbadensis Leaf Juice.

PURPOSE

Anitseptic

Directions

- Read the entire label before using this product.
- Place enough product on your palm to thoroughly cover your hands.
- Rub hands together briskly until dry.

Uses

- Hand sanitizer to reduce microorganisms on the skin
- Use thi product when soap and water are not available

- KEEP OUT OF REACH OF CHILDREN